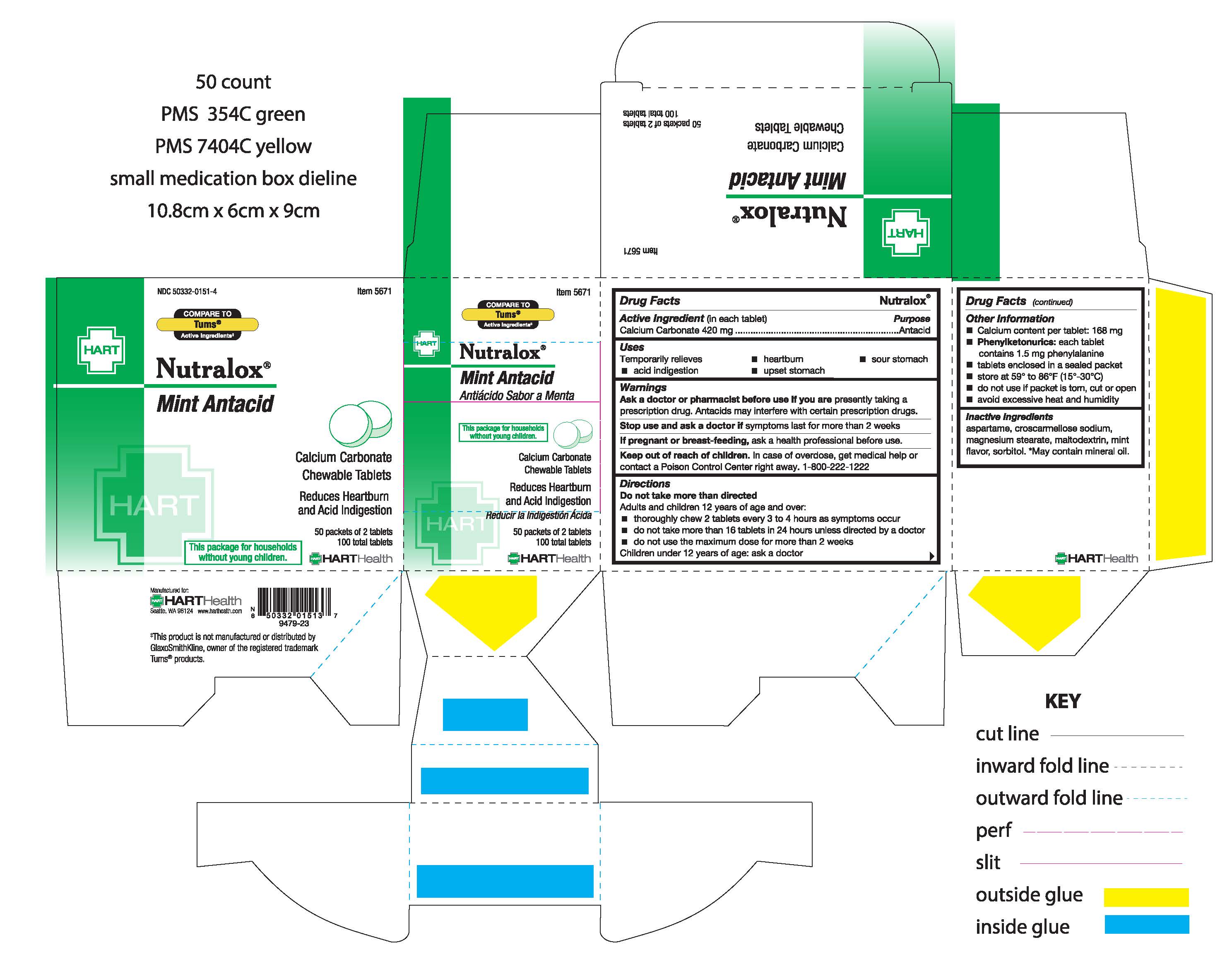 DRUG LABEL: NUTRALOX
NDC: 50332-0151 | Form: TABLET, CHEWABLE
Manufacturer: HART Health
Category: otc | Type: HUMAN OTC DRUG LABEL
Date: 20251231

ACTIVE INGREDIENTS: CALCIUM CARBONATE 420 mg/1 1
INACTIVE INGREDIENTS: ASPARTAME; CROSCARMELLOSE SODIUM; MAGNESIUM STEARATE; MALTODEXTRIN; MINERAL OIL; SORBITOL

NUTRALOX

Active Ingredient (in each tablet): Calcium Carbonate 420 mg

Purpose: Antacid

INDICATIONS AND USAGE

Uses: Temporarily relieves

- heartburn
- sour stomach
- acid indigestion
- upset stomach

Warnings:

Ask a doctor or pharmacist before use if you are presently taking a prescription drug. Antacids may interfere with certain prescription drugs.

Stop use and ask a doctor if symptoms last for more than 2 weeks

PREGNANCY OR BREAST FEEDING

If pregnant or breast-feeding, ask a health professional before use

Keep out of reach of children. In case of overdose, get medical help or contact a Poison Control Center right away. 1-800-222-1222

Directions:

Do not take more than directed

Adults and children 12 years of age and over:

- thoroughly chew 2 tablets every 3 to 4 hours as symptoms occur
- do not take more than 16 tablets in 24 hours unless directed by a doctor
- do not use the maximum dose for more than 2 weeks

Children under 12 years of age: ask a doctor

Other information:

- Calcium content per tablet: 168mg
- phenylketonurics: each tablet may contain 1.5 mg phenylalanine
- tablets enclosed in a sealed packet
- do not use if packet is torn, cut or open
- store at 59° to 86°F (15°-30°C)
- avoid excessive heat and humidity

Inactive ingredients

aspartame, croscarmellose sodium, magnesium stearate, maltodextrin, mint flavor, sorbitol

May contain mineral oil